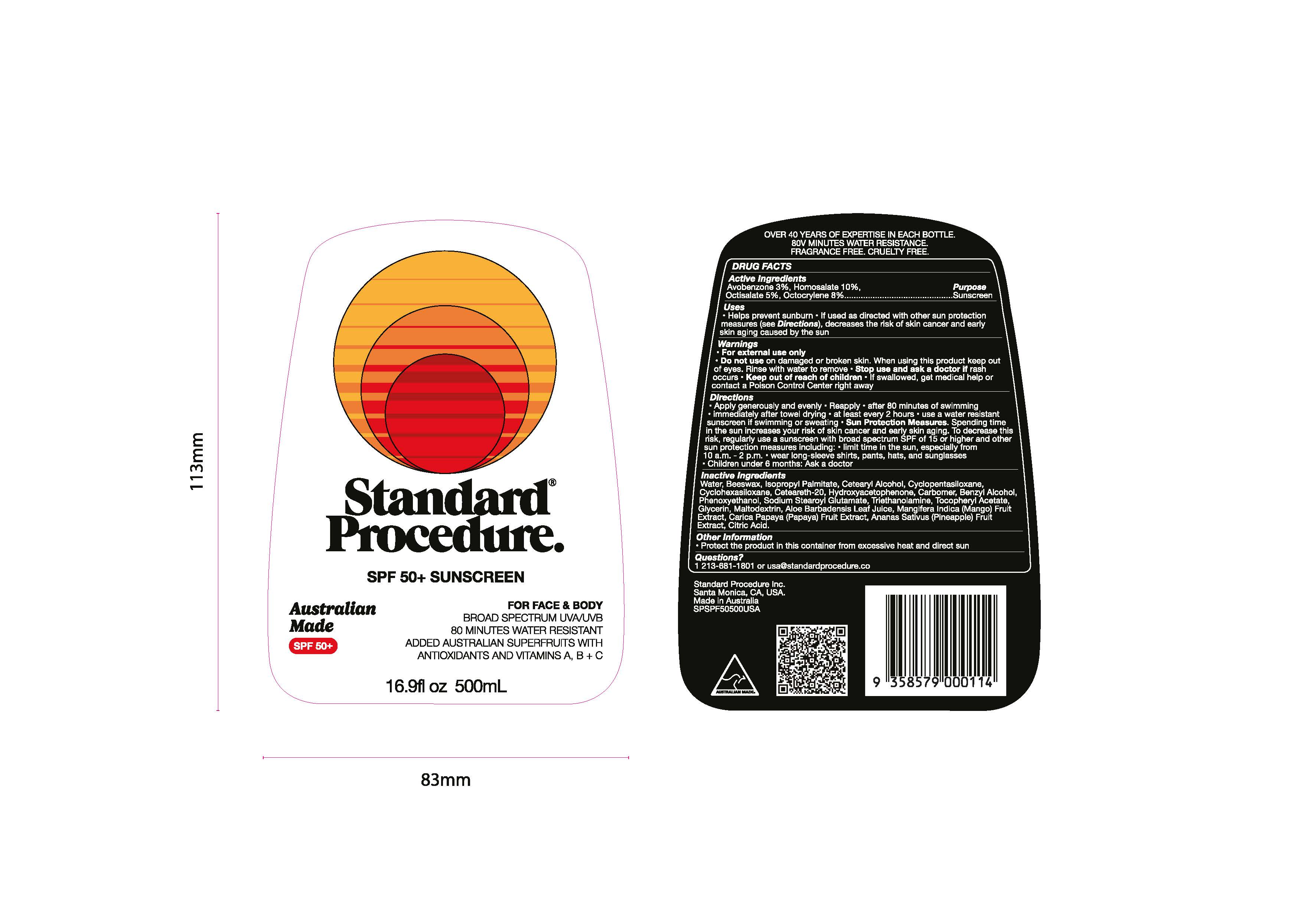 DRUG LABEL: Standard Procedure SPF 50 Sunscreen Face and Body
NDC: 70157-027 | Form: LOTION
Manufacturer: Baxter Laboratories
Category: otc | Type: HUMAN OTC DRUG LABEL
Date: 20250512

ACTIVE INGREDIENTS: AVOBENZONE 3 g/100 mL; OCTISALATE 5 g/100 mL; HOMOSALATE 10 g/100 mL; OCTOCRYLENE 8 g/100 mL
INACTIVE INGREDIENTS: PAPAYA; BEESWAX; CETEARETH-20; TRIETHANOLAMINE; CYCLOMETHICONE 5; CYCLOMETHICONE 6; PHENOXYETHANOL; ALOE VERA LEAF JUICE; CARBOMER; MALTODEXTRIN; CITRIC ACID; CETOSTEARYL ALCOHOL; HYDROXYACETOPHENONE; BENZYL ALCOHOL; SODIUM STEAROYL GLUTAMATE; MANGO; WATER; ISOPROPYL PALMITATE; PINEAPPLE; .ALPHA.-TOCOPHEROL ACETATE; GLYCERIN

Standard Procedure SPF 50+ Sunscreen Face and Body Lotion

Active Ingredients Purpose

Avobenzone3%, Homosalate 10%, Octisalate 5%, Octocrylene 8% Sunscreen

Purpose

Sunscreen

Uses

- Helps prevent sunburn
- if used as directed with other sun protection measures (see Directions), decreases the risk of skin cancer and early skin aging caused by the sun

- Keep out of reach of children
- If swallowed, get medical help or contact a Poison Control Center right away

Stop use and ask a doctor if rash occurs

Warnings

For external use only

Do not use on damaged or broken skin. When using this product keep out of eyes. Rinse with water to remove.

Directions

- Apply generously and evenly
- Reapply
- after 80 minutes of swimming
- Immediately after towel drying
- at least every 2 hours
- use a water resistant sunscreen if swimming or sweating
- Sun Protection Measures. Spending time in the sun increases your risk of skin cancer and early skin aging.To decrease this risk, regularly use a sunscreen with broad spectrum SPF 15 or higher and other sun protection measures including:
- limit time in the sun, especially from 10 a.m. to 2 p.m.
- wear long-sleeve shirts, pants, hats, and sunglasses
- Children under 6 months: ask a doctor

Inactive Ingredients

Water, Beeswax, Isopropyl Palmitate, Cetearyl Alcohol, Cyclopentasiloxane, Cyclohexasiloxane, Ceteareth-20, Hydroxyacetophenone, Carbomer, Benzyl alcohol, Phenoxyethanol, Sodium Stearoyl Glutamate, Triethanolamine, Tocopheryl Acetate, Glycerin, Maltodextrin, Aloe Barbadensis Leaf Juice, Mangifera Indica (Mango) Fruit Extract, Carica Papaya (Papaya) Fruit Extract, Ananas Sativus (Pineapple) Fruit Extract, Citric Acid.

Other information

- protect the product in this container from excessive heat and direct sun

Questions?

1 213-681-1801 or usa@standardprocedure.co

PACKAGE LABEL

Standard Procedure

SPF 50+ sunscreen

For face and body

Broad Spectrum UVA/UVB

80 Minutes Water Resistant

Added Australian Superfruits with Antioxidants and Vitamins A, B + C